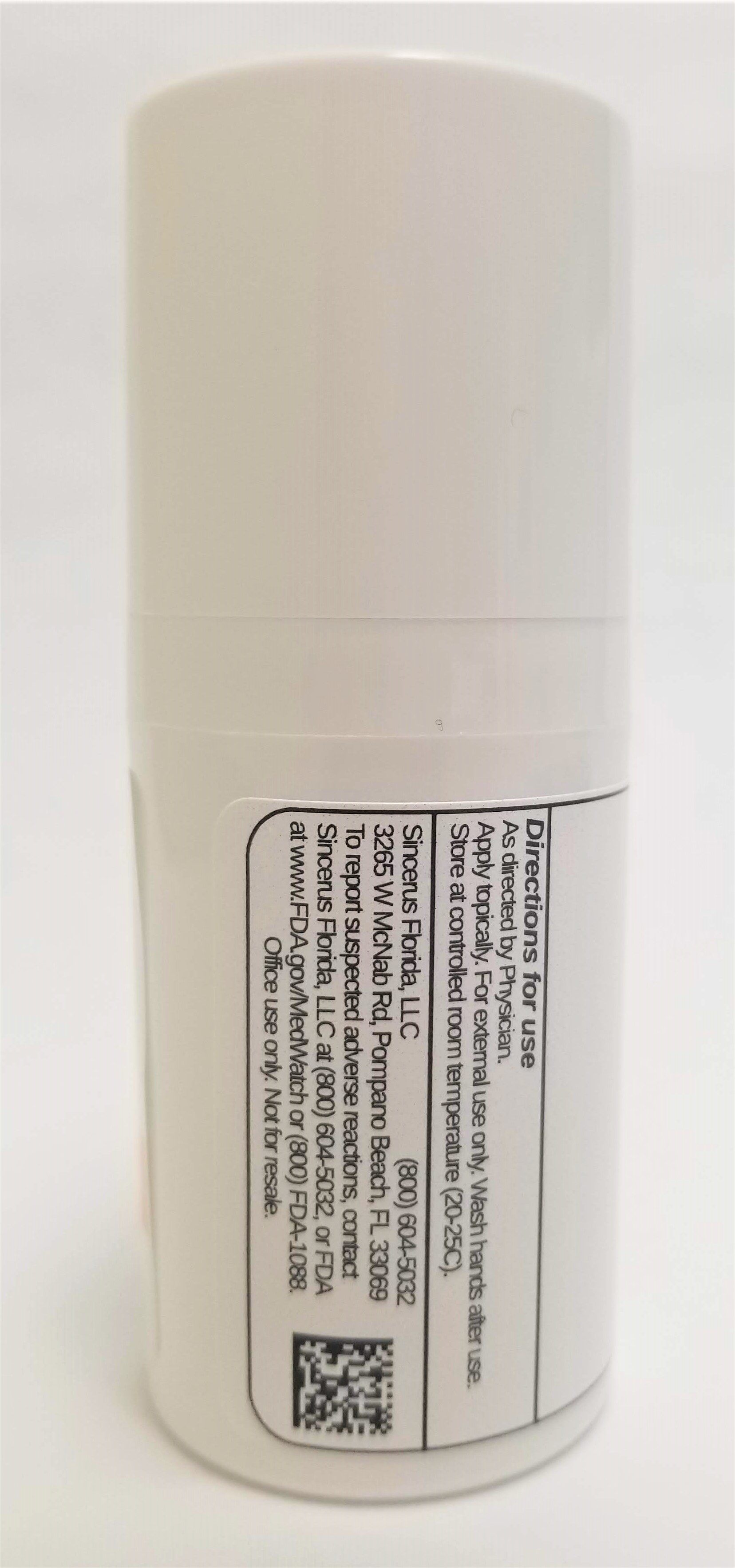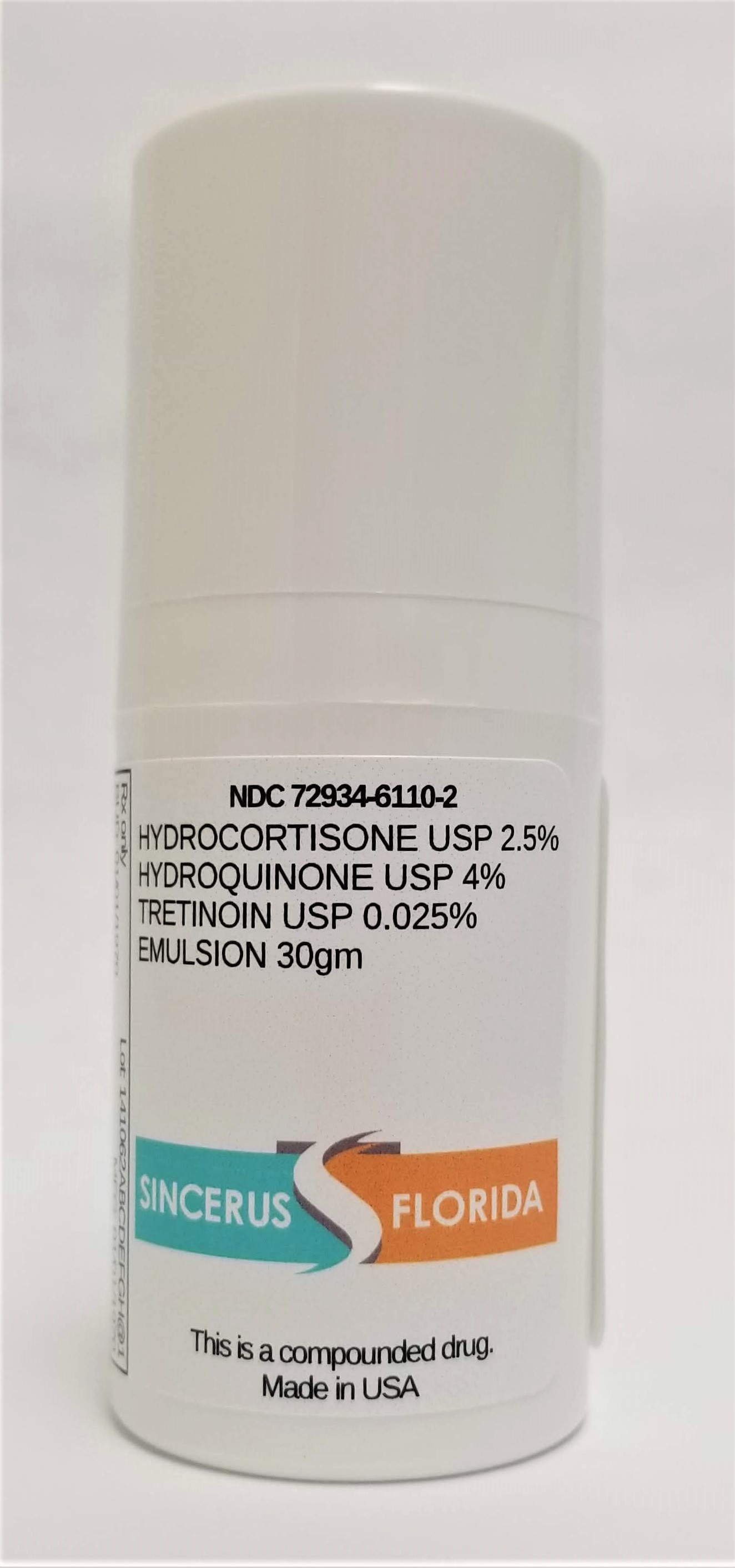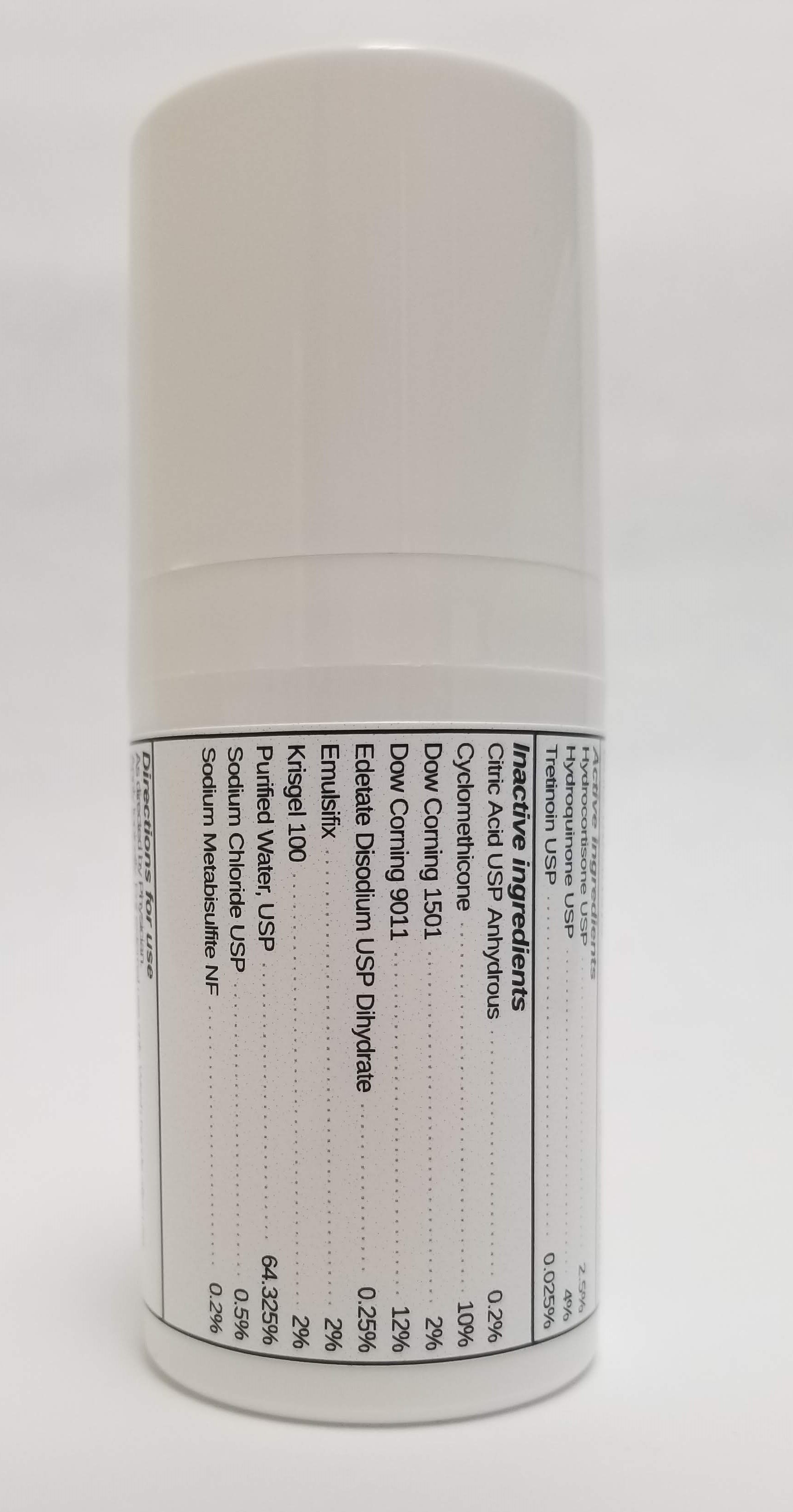 DRUG LABEL: HYDROCORTISONE 2.5% / HYDROQUINONE 4% / TRETINOIN 0.025%,
NDC: 72934-6110 | Form: EMULSION
Manufacturer: Sincerus Florida, LLC
Category: prescription | Type: HUMAN PRESCRIPTION DRUG LABEL
Date: 20190517

ACTIVE INGREDIENTS: HYDROQUINONE 4 g/100 g; HYDROCORTISONE 2.5 g/100 g

HYDROCORTISONE 2.5% / HYDROQUINONE 4% / TRETINOIN 0.025%,